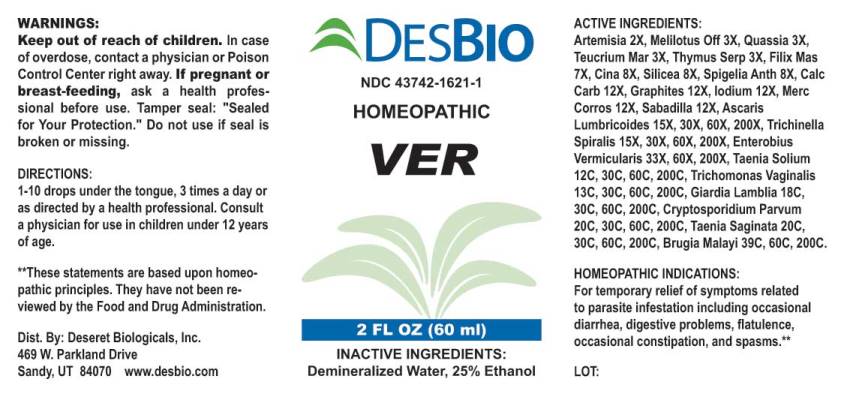 DRUG LABEL: Ver
NDC: 43742-1621 | Form: LIQUID
Manufacturer: Deseret Biologicals, Inc.
Category: homeopathic | Type: HUMAN OTC DRUG LABEL
Date: 20210628

ACTIVE INGREDIENTS: ARTEMISIA VULGARIS ROOT 2 [hp_X]/1 mL; MELILOTUS OFFICINALIS TOP 3 [hp_X]/1 mL; QUASSIA AMARA WOOD 3 [hp_X]/1 mL; TEUCRIUM MARUM 3 [hp_X]/1 mL; THYMUS SERPYLLUM 3 [hp_X]/1 mL; DRYOPTERIS FILIX-MAS ROOT 7 [hp_X]/1 mL; ARTEMISIA CINA PRE-FLOWERING TOP 8 [hp_X]/1 mL; SILICON DIOXIDE 8 [hp_X]/1 mL; SPIGELIA ANTHELMIA 8 [hp_X]/1 mL; OYSTER SHELL CALCIUM CARBONATE, CRUDE 12 [hp_X]/1 mL; GRAPHITE 12 [hp_X]/1 mL; IODINE 12 [hp_X]/1 mL; MERCURIC CHLORIDE 12 [hp_X]/1 mL; SCHOENOCAULON OFFICINALE SEED 12 [hp_X]/1 mL; ASCARIS LUMBRICOIDES 15 [hp_X]/1 mL; TRICHINELLA SPIRALIS 15 [hp_X]/1 mL; ENTEROBIUS VERMICULARIS 33 [hp_X]/1 mL; TAENIA SOLIUM 12 [hp_C]/1 mL; TRICHOMONAS VAGINALIS 13 [hp_C]/1 mL; GIARDIA LAMBLIA 18 [hp_C]/1 mL; CRYPTOSPORIDIUM PARVUM 20 [hp_C]/1 mL; TAENIA SAGINATA 20 [hp_C]/1 mL; BRUGIA MALAYI 39 [hp_C]/1 mL
INACTIVE INGREDIENTS: WATER; ALCOHOL

Drug Facts:

ACTIVE INGREDIENTS:

Artemisia Vulgaris 2X, Melilotus Officinalis 3X, Quassia (Amara) 3X, Teucrium Marum 3X, Thymus Serpyllum 3X, Filix Mas 7X, Cina 8X, Silicea 8X, Spigelia Anthelmia 8X, Calcarea Carbonica 12X, Graphites 12X, Iodium 12X, Mercurius Corrosivus 12X, Sabadilla 12X, Ascaris Lumbricoides 15X, 30X, 60X, 200X, Trichinella Spiralis 15X, 30X, 60X, 200X, Enterobius Vermicularis 33X, 60X, 200X, Taenia Solium 12C, 30C, 60C, 200C, Trichomonas Vaginalis 13C, 30C, 60C, 200C, Giardia Lamblia 18C, 30C, 60C, 200C, Cryptosporidium Parvum 20C, 30C, 60C, 200C, Taenia Saginata 20C, 30C, 60C, 200C, Brugia Malayi 39C, 60C, 200C.

HOMEOPATHIC INDICATIONS:

For temporary relief of symptoms related to parasite infestation including occasional diarrhea, digestive problems, flatulence, occasional constipation, and spasms.**
**These statements are based upon homeopathic principles. They have not been reviewed by the Food and Drug Administration.

WARNINGS:

Keep out of reach of children. In case of overdose, contact a physician or Poison Control Center right away.

If pregnant or breast-feeding, ask a health professional before use.

Tamper seal: "Sealed for Your Protection." Do not use if seal is broken or missing.

Keep out of reach of children. In case of overdose, contact a physician or Poison Control Center right away.

DIRECTIONS:

1-10 drops under the tongue, 3 times a day or as directed by a health professional. Consult a physician for use in children under 12 years of age.

HOMEOPATHIC INDICATIONS:

For temporary relief of symptoms related to parasite infestation including occasional diarrhea, digestive problems, flatulence, occasional constipation, and spasms.**
**These statements are based upon homeopathic principles. They have not been reviewed by the Food and Drug Administration.

INACTIVE INGREDIENTS:

Demineralized Water, 25% Ethanol

QUESTIONS:

Dist. By: Deseret Biologicals, Inc.

469 W. Parkland Drive

Sandy, UT 84070 www.desbio.com

PACKAGE LABEL DISPLAY:

DESBIO

NDC 43742-1621-1

HOMEOPATHIC

VER

2 FL OZ (30 ml)